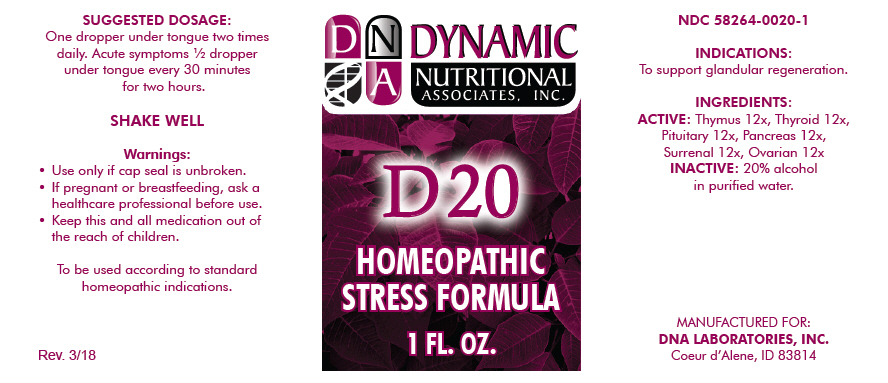 DRUG LABEL: D-20
NDC: 58264-0020 | Form: SOLUTION/ DROPS
Manufacturer: DNA Labs, Inc.
Category: homeopathic | Type: HUMAN OTC DRUG LABEL
Date: 20250113

ACTIVE INGREDIENTS: BOS TAURUS THYMUS 12 [hp_X]/1 mL; THYROID, UNSPECIFIED 12 [hp_X]/1 mL; BOS TAURUS PITUITARY GLAND, POSTERIOR 12 [hp_X]/1 mL; BOS TAURUS PANCREAS 12 [hp_X]/1 mL; BOS TAURUS ADRENAL GLAND 12 [hp_X]/1 mL; BOS TAURUS OVARY 12 [hp_X]/1 mL
INACTIVE INGREDIENTS: ALCOHOL; WATER

D-20

NDC 58264-0020-1

INDICATIONS

PURPOSE

To support glandular regeneration.

INGREDIENTS

ACTIVE

Thymus 12x, Thyroid 12x, Pituitary 12x, Pancreas 12x, Surrenal 12x, Ovarian 12x

INACTIVE

20% alcohol in purified water.

SUGGESTED DOSAGE

One dropper under tongue two times daily. Acute symptoms ½ dropper under tongue every 30 minutes for two hours.

STORAGE AND HANDLING

SHAKE WELL

Warnings

- Use only if cap seal is unbroken.

PREGNANCY OR BREAST FEEDING

- If pregnant or breastfeeding, ask a healthcare professional before use.

KEEP OUT OF REACH OF CHILDREN

- Keep this and all medication out of the reach of children.

To be used according to standard homeopathic indications.

PRINCIPAL DISPLAY PANEL - 1 FL. OZ. Bottle Label

DYNAMIC
NUTRITIONAL
ASSOCIATES, INC.

D 20

HOMEOPATHIC
STRESS FORMULA

1 FL. OZ.